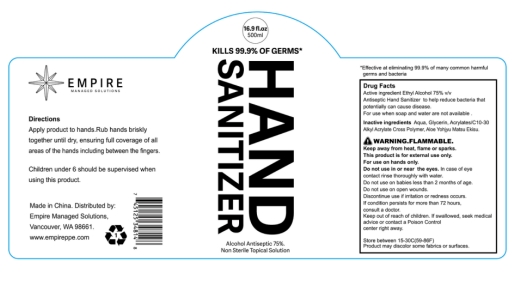 DRUG LABEL: Hand Sanitizer
NDC: 54237-004 | Form: LIQUID
Manufacturer: Guangzhou Daieme Cosmetic Co,.Ltd
Category: otc | Type: HUMAN OTC DRUG LABEL
Date: 20201008

ACTIVE INGREDIENTS: ALCOHOL 375 mL/500 mL
INACTIVE INGREDIENTS: ALOE; GLYCERIN; CARBOMER INTERPOLYMER TYPE A (ALLYL SUCROSE CROSSLINKED); WATER; TOCOPHEROL

DOSAGE AND ADMINISTRATION

Do not store above 105°F

ACTIVE INGREDIENT

Alcohol

keep out of reach of children

WARNINGS

For external use only: hands Flammable keep away from fire or flame.

INACTIVE INGREDIENT

Acrylates/C10-30 Alkyl acrylate Crosspolymer, Aloe Extract,Glycerin,Tocopherol,Water

PURPOSE

Disinfection
Sterilization
No Rinseing

INDICATIONS AND USAGE

wet hands thoroughly with product and allow to dry without wiping.